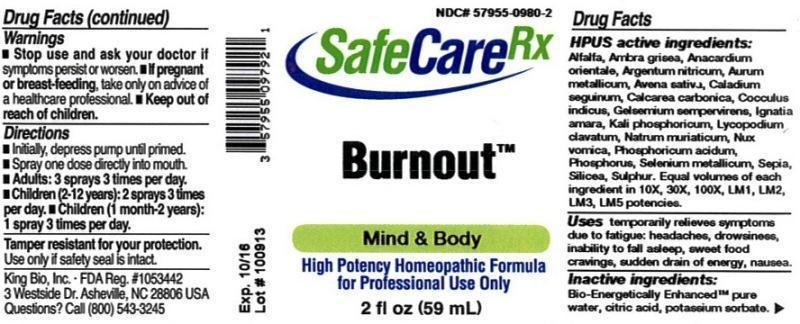 DRUG LABEL: Burnout
NDC: 57955-0980 | Form: LIQUID
Manufacturer: King Bio Inc.
Category: homeopathic | Type: HUMAN OTC DRUG LABEL
Date: 20131113

ACTIVE INGREDIENTS: ALFALFA 10 [hp_X]/59 mL; AMBERGRIS 10 [hp_X]/59 mL; SEMECARPUS ANACARDIUM JUICE 10 [hp_X]/59 mL; SILVER NITRATE 10 [hp_X]/59 mL; GOLD 10 [hp_X]/59 mL; AVENA SATIVA FLOWERING TOP 10 [hp_X]/59 mL; DIEFFENBACHIA SEGUINE 10 [hp_X]/59 mL; OYSTER SHELL CALCIUM CARBONATE, CRUDE 10 [hp_X]/59 mL; ANAMIRTA COCCULUS SEED 10 [hp_X]/59 mL; GELSEMIUM SEMPERVIRENS ROOT 10 [hp_X]/59 mL; STRYCHNOS IGNATII SEED 10 [hp_X]/59 mL; POTASSIUM PHOSPHATE, DIBASIC 10 [hp_X]/59 mL; LYCOPODIUM CLAVATUM SPORE 10 [hp_X]/59 mL; SODIUM CHLORIDE 10 [hp_X]/59 mL; STRYCHNOS NUX-VOMICA SEED 10 [hp_X]/59 mL; PHOSPHORIC ACID 10 [hp_X]/59 mL; PHOSPHORUS 10 [hp_X]/59 mL; SELENIUM 10 [hp_X]/59 mL; SEPIA OFFICINALIS JUICE 10 [hp_X]/59 mL; SILICON DIOXIDE 10 [hp_X]/59 mL; SULFUR 10 [hp_X]/59 mL
INACTIVE INGREDIENTS: WATER; CITRIC ACID MONOHYDRATE; POTASSIUM SORBATE

Burnout™

Warnings

- Stop use and ask your doctor if symptoms persist or worsen.
- If pregnant or breast-feeding, take only on advice of a healthcare professional.

Keep out of reach of children

DOSAGE AND ADMINISTRATION

- Initially, depress pump until primed.
- Spray one dose directly into mouth.
- Adults: 3 sprays 3 times per day.
- Children (2-12 years): 2 sprays 3 times per day.
- Children (1 month-2 years): 1 spray 3 times per day.

OTHER SAFETY INFORMATION

Tamper resistant for your protection. Use only if safety seal is intact.

ACTIVE INGREDIENT

HPUS active ingredients: Alfalfa, Ambra grisea, Anacardium orientale, Argentum nitricum, Aurum metallicum, Avena sativa, Caladium seguinum, Calcarea carbonica, Cocculus indicus, Gelsemium sempervirens, Ignatia amara, Kali phosphoricum, Lycopodium clavatum, Natrum muriaticum, Nux vomica, Phosphoricum acidum, Phosphorus, Selenium metallicum, Sepia, Silicea, Sulphur. Equal volumes of each ingredient in 10X, 30X, 100X, LM1, LM2, LM3, LM5 potencies.

PURPOSE

Uses temporarily relieves symptoms due to fatigue: headaches, drowsiness, inability to fall asleep, sweet food cravings, sudden drain of energy, nausea.

Inactive Ingredients:

Bio-Energetically Enhanced™ pure water, citric acid and potassium sorbate.

INDICATIONS AND USAGE

Uses temporarily relieves symptoms due to fatigue:

- headaches
- drowsiness
- inability to fall asleep
- sweet food cravings
- sudden drain of energy
- nausea